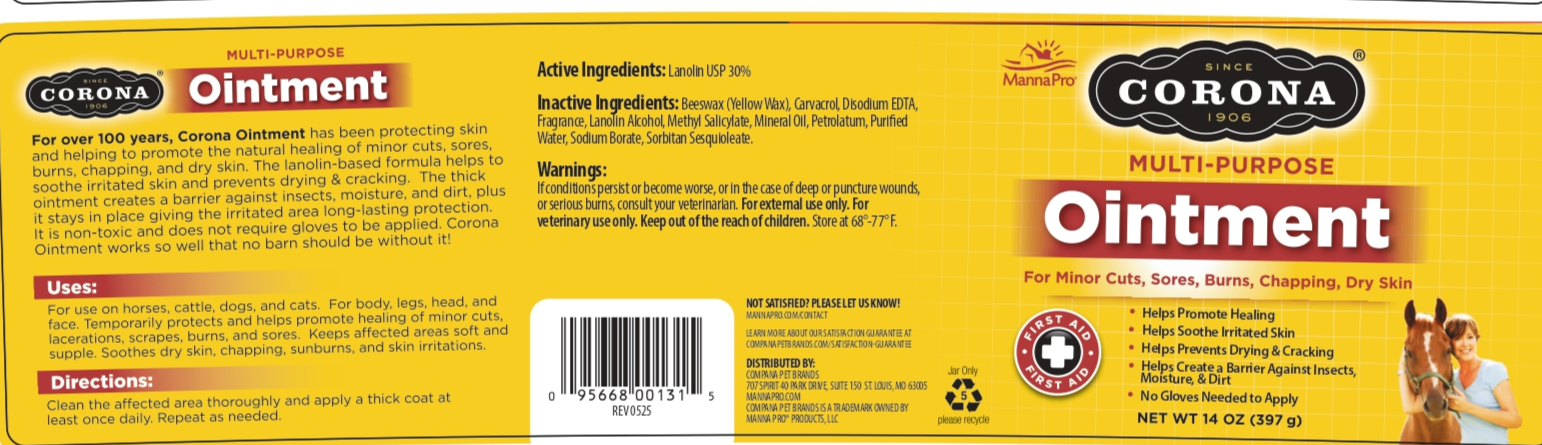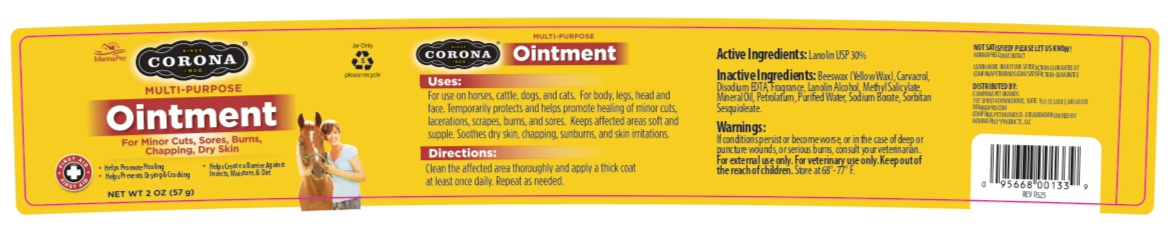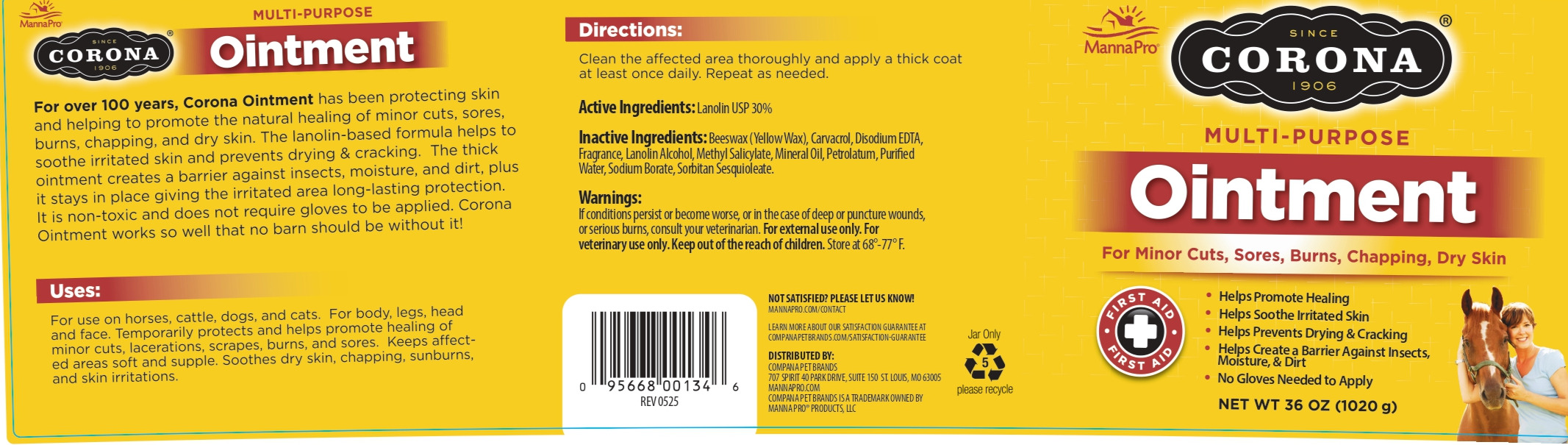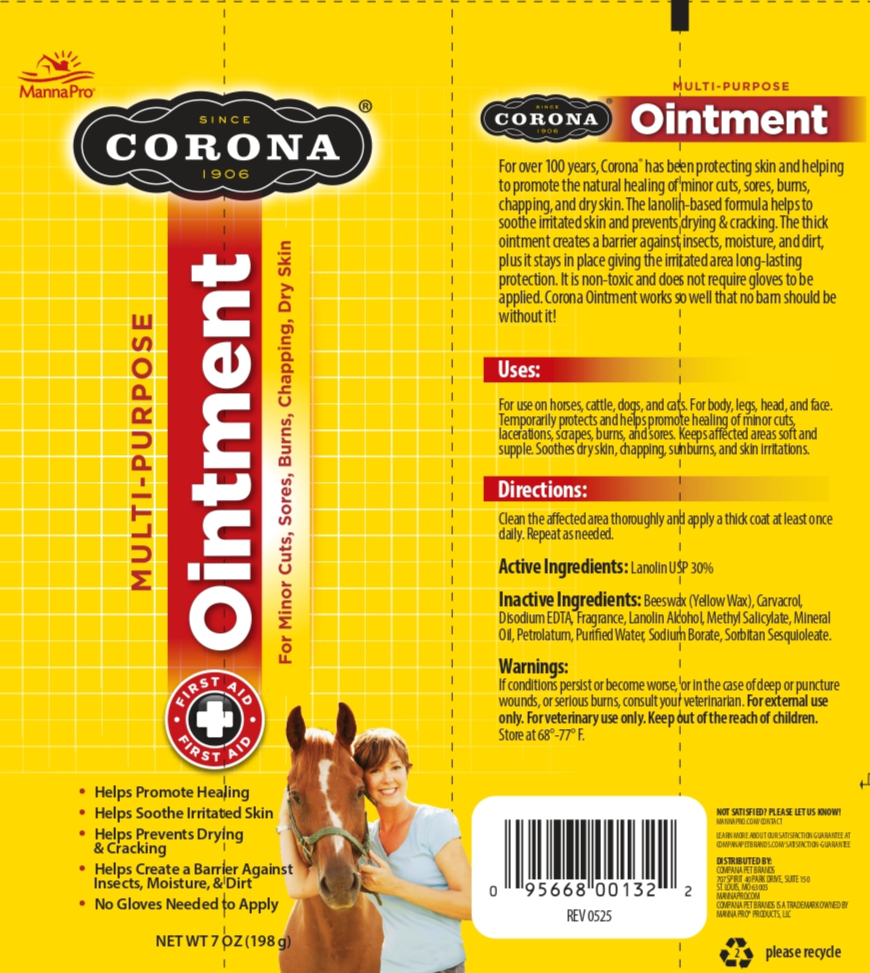 DRUG LABEL: CORONA MULTI-PURPOSE
NDC: 86077-3000 | Form: OINTMENT
Manufacturer: Manna Pro Products LLC
Category: animal | Type: OTC ANIMAL DRUG LABEL
Date: 20251217

ACTIVE INGREDIENTS: LANOLIN 30 g/100 g
INACTIVE INGREDIENTS: YELLOW WAX; CARVACROL; EDETATE DISODIUM; LANOLIN ALCOHOL; METHYL SALICYLATE; MINERAL OIL; PETROLATUM; WATER; SODIUM BORATE; SORBITAN SESQUIOLEATE

CORONA MULTI-PURPOSE OINTMENT

Active Ingredients: Lanolin USP 30%

Purpose - Skin Protectant

Uses:

For use on horses, cattle, dogs, and cats. For body, legs, head and face. Temporarily protects and helps promote healing of minor cuts, lacerations, scrapes, burns and sores. Keeps affected areas soft and supple. Soothes dry skin, chapping, sunburns, and skin irritations.

Warnings:

If conditions persist or become worse, or in the case of deep or puncture wounds,
or serious burns, consult your veterinarian. For external use only. For
veterinary use only.

Keep out of the reach of children.

DOSAGE AND ADMINISTRATION

Clean the affected area thoroughly and apply a thick coat at least once daily. Repeat as needed.

Other Information:

Store at 68-77 Degrees F.

Inactive Ingredients

Beeswax (Yellow Wax), Carvacrol, Disodium EDTA, Fragrance, Lanolin Alcohol, Methyl Salicylate, Mineral Oil, Petrolatum, Purified Water, Sodium Borate, Sorbitan Sesquioleate

QUESTIONS

NOT SATISFIED? PLEASE LET US KNOW!
MANNAPRO.COM/CONTACT

PACKAGE LABEL

SINCE 1906

CORONA

MULTI-PURPOSE OINTMENT

For Minor Cuts, Sores, Burns, Chapping, Dry Skin

- Helps Promote Healing

- Helps Soothe Irritated Skin

- Helps Prevent Drying & Cracking

- Helps Create a Barrier Against Insects, Moisture, & Dirt

- No Gloves Needed to APply

CORONAMULTI-PURPOSE OINTMENT

For over 100 years, Corona Ointment has been protecting skin and helping to promote the natural healing of minor cuts, sores, burns, chapping, and dry skin. The lanolin-based formula helps to soothe irritated skin and prevent drying and cracking. The thick ointment creates a barrier against insects, moisture, and dirt, plus it stays in place giving the irritated area long-lasting protection. It is non-toxic and does not require gloves to be aqpplied. Corona Ointment works so well that no barn should be without it!

LEARN MORE ABOUT OUR SATISFACTION GUARANTEE AT

COMPANAPETBRANDS.COM/SATISFACTION-GUARANTEE

DISTRIBUTED BY:

COMPANA PETS BRANDS

707 SPIRIT 40 PARK DRIVE, SUITE 150, ST. LOUIS, MO 63005

MANNAPRO.COM

COMPANA PET BRANDS IS A TRADEMARK OWNED BY

MANNA PRO PRODUCTS, LLC